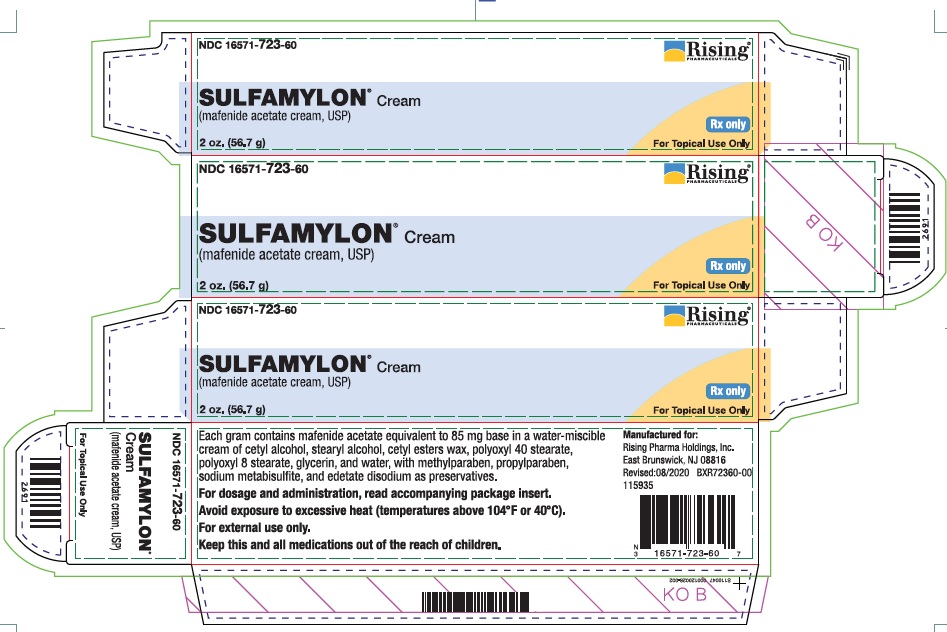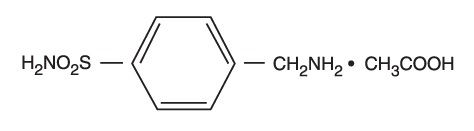 DRUG LABEL: SULFAMYLON
NDC: 16571-723 | Form: CREAM
Manufacturer: Rising Pharma Holdings, Inc.
Category: prescription | Type: Human Prescription Drug Label
Date: 20230703

ACTIVE INGREDIENTS: MAFENIDE ACETATE 85 mg/1 g
INACTIVE INGREDIENTS: CETYL ALCOHOL; STEARYL ALCOHOL; POLYOXYL 40 STEARATE; PEG-8 STEARATE; GLYCERIN; WATER; METHYLPARABEN; PROPYLPARABEN; SODIUM METABISULFITE; EDETATE DISODIUM

DESCRIPTION

SULFAMYLON Cream is a soft, white, nonstaining, water-miscible, anti-infective cream for topical administration to burn wounds.
SULFAMYLON Cream spreads easily, and can be washed off readily with water. It has a slight acetic odor. Each gram of SULFAMYLON Cream contains mafenide acetate equivalent to 85 mg of the base. The cream vehicle consists of cetyl alcohol, steryl alcohol, cetyl esters wax, polyoxyl 40 stearate, polyoxyl 8 stearate, glycerin, and water, with methylparaben, propylparaben, sodium metabisulfite, and edetate disodium as preservatives.
Chemically, mafenide acetate is α-Amino-ρ-toluenesulfonamide monoacetate and has the following structural formula:

CLINICAL PHARMACOLOGY

SULFAMYLON Cream, applied topically produces a marked reduction in the bacterial population present in the avascular tissues of second- and third-degree burns. Reduction in bacterial growth after application of SULFAMYLON Cream has also been reported to permit spontaneous healing of deep partial-thickness burns, and thus prevent conversion of burn wounds from partial-thickness to full-thickness. It should be noted, however, that delayed eschar separation has occurred in some cases.
Absorption and Metabolism
Applied topically, SULFAMYLON Cream diffuses through devascularized areas, is absorbed, and rapidly converted to a metabolite (ρ-carboxybenzenesulfonamide) which is cleared through the kidneys. SULFAMYLON is active in the presence of pus and serum, and its activity is not altered by changes in the acidity of the environment.
Antibacterial Activity
SULFAMYLON exerts bacteriostatic action against many gram-negative and gram-positive organisms, including Pseudomonas aeruginosa and certain strains of anaerobes.

INDICATIONS AND USAGE

SULFAMYLON Cream is a topical agent indicated for adjunctive therapy of patients with second- and third-degree burns.

CONTRAINDICATIONS

SULFAMYLON is contraindicated in patients who are hypersensitive to it. It is not known whether there is cross sensitivity to other sulfonamides.

WARNINGS

Fatal hemolytic anemia with disseminated intravascular coagulation, presumably related to a glucose-6-phosphate dehydrogenase deficiency, has been reported following therapy with SULFAMYLON Cream.
Contains sodium metabisulfite, a sulfite that may cause allergic-type reactions including anaphylactic symptoms and life-threatening or less severe asthmatic episodes in certain susceptible people. The overall prevalence of sulfite sensitivity in the general population is unknown and probably low. Sulfite sensitivity is seen more frequently in asthmatic than in nonasthmatic people.

PRECAUTIONS

SULFAMYLON and its metabolite, ρ-carboxybenzenesulfonamide, inhibit carbonic anhydrase, which may result in metabolic acidosis, usually compensated by hyperventilation. In the presence of impaired renal function, high blood levels of SULFAMYLON and its metabolite may exaggerate the carbonic anhydrase inhibition. Therefore, close monitoring of acid-base balance is necessary, particularly in patients with extensive second-degree or partial-thickness burns and in those with pulmonary or renal dysfunction. Some burn patients treated with SULFAMYLON Cream have also been reported to manifest an unexplained syndrome of marked hyperventilation with resulting respiratory alkalosis (slightly alkaline blood pH, low arterial pCO2 , and decreased total CO2); change in arterial pO2 is variable. The etiology and significance of these findings are unknown.
Mafenide acetate cream should be used with caution in burn patients with acute renal failure.
SULFAMYLON Cream should be administered with caution to patients with history of hypersensitivity to mafenide. It is not known whether there is cross sensitivity to other sulfonamides.
Fungal colonization in and below eschar may occur concomitantly with reduction of bacterial growth in the burn wound. However, fungal dissemination through the infected burn wound is rare.
Carcinogenesis, Mutagenesis, Impairment of Fertility
No long-term animal studies have been performed to evaluate the drug’s potential in these areas.
Pregnancy
Animal reproduction studies have not been conducted with SULFAMYLON. It is also not known whether SULFAMYLON can cause fetal harm when administered to a pregnant woman or can affect reproduction capacity. Therefore, the preparation is not recommended for the treatment of a women of childbearing potential, unless the burned area covers more than 20% of the total body surface, or the need for the therapeutic benefit of SULFAMYLON Cream is, in the physician’s judgment, greater than the possible risk to the fetus.
Nursing Mothers
It is not known whether mafenide acetate is excreted in human milk. Because many drugs are excreted in human milk and because of the potential for serious adverse reaction in nursing infants from SULFAMYLON, a decision should be made whether to discontinue nursing or to discontinue the drug, taking into account the importance of the drug to the mother.
Pediatric Use
Same as for adults. (See DOSAGE AND ADMINISTRATION.)

ADVERSE REACTIONS

It is frequently difficult to distinguish between an adverse reaction to SULFAMYLON Cream and the effect of a severe burn. A single case of bone marrow depression and a single case of acute attack of porphyria have been reported following therapy with SULFAMYLON Cream. Fatal hemolytic anemia with disseminated intravascular coagulation, presumably related to a glucose-6-phosphate dehydrogenase deficiency, has been reported following therapy with SULFAMYLON Cream.
Dermatologic: The most frequently reported reaction was pain on application or a burning sensation. Rare occurrences are excoriation of new skin and bleeding of skin.
Allergic: Rash itching, facial edema, swelling, hive, blisters, erythema, and eosinophilia.
Respiratory: Tachypnea or hyperventilation, decrease in arterial pCO2.
Metabolic: Acidosis, increase in serum chloride.
Accidental ingestion of SULFAMYLON Cream has been reported to cause diarrhea.
To report SUSPECTED ADVERSE REACTIONS, contact Rising Pharma Holdings, Inc. at 1-844-874-7464 or FDA at 1-800-FDA-1088 or www.fda.gov/medwatch.

DOSAGE AND ADMINISTRATION

Prompt institution of appropriate measures for controlling shock and pain is of prime importance. The burn wounds are then cleansed and debrided, and SULFAMYLON Cream is applied with a sterile gloved hand. Satisfactory results can be achieved with application of the cream once or twice daily, to a thickness of approximately 1/16 inch; thicker application is not recommended. The burned areas should be covered with SULFAMYLON Cream at all times. Therefore, whenever necessary, the cream should be reapplied to any areas from which it has been removed (e.g., by patient activity). The routine of administration can be accomplished in minimal time, since dressings usually are not required, if individual patient demands make them necessary, however, only a thin layer of dressings should be used.

When feasible, the patient should be bathed daily to aid in debridement. A whirlpool bath is particularly helpful, but the patient may be bathed in bed or in a shower.

The duration of therapy with SULFAMYLON Cream depends on each patient’s requirements. Treatment is usually continued until healing is progressing well or until the burn site is ready for grafting. SULFAMYLON Cream should not be withdrawn from the therapeutic regimen while there is the possibility of infection. However, if allergic manifestations occur during treatment with SULFAMYLON Cream, discontinuation of treatment should be considered.

If acidosis occurs and becomes difficult to control, particularly in patients with pulmonary dysfunction, discontinuing therapy SULFAMYLON Cream for 24 to 48 hours while continuing fluid therapy may aid in restoring acid-base balance.

HOW SUPPLIED

16 oz. Plastic Jar (453.6 g) - NDC 16571-723-48
4 oz. Tube (113.4 g) - NDC 16571-723-12
2 oz. Tube (56.7 g) - NDC 16571-723-60
Avoid exposure to excessive heat (temperature above 104° F or 40° C).
For External Use Only.
Keep this and all medications out of the reach of children.
Rx only
Manufactured for:
Rising Pharma Holdings, Inc.
East Brunswick, NJ 08816
Revised: 08/2020
PIR72348-00

PACKAGE LABEL.PRINCIPAL DISPLAY PANEL

NDC 16571-723-60 Rising®
SULFAMYLON® Cream
(mafenide acetate cream, USP)
Rx only
2 oz. (56.7 g) For Topical Use Only
Each gram contains mafenide acetate equivalent to 85 mg base in a water-miscible cream of cetyl alcohol, stearyl alcohol, cetyl esters wax, polyoxyl 40 stearate, polyoxyl 8 stearate, glycerin, and water, with methylparaben, propylparaben, sodium metabisulfite, and edetate disodium as preservatives.
For dosage and administration, read accompanying package insert.
Avoid exposure to excessive heat (temperatures above 104°F or 40°C).
For external use only.
Keep this and all medications out of the reach of children.